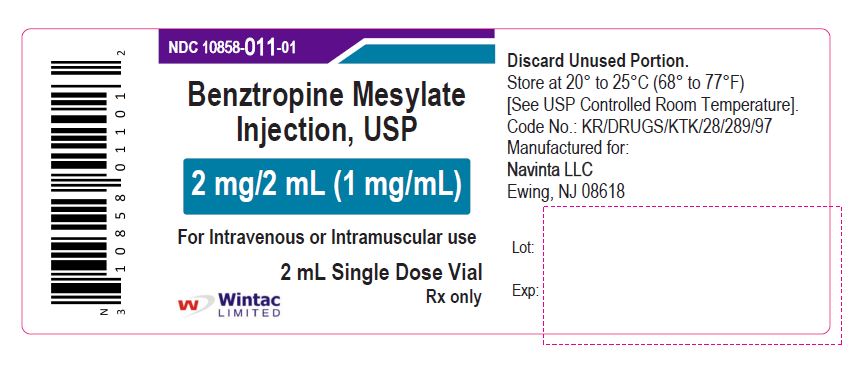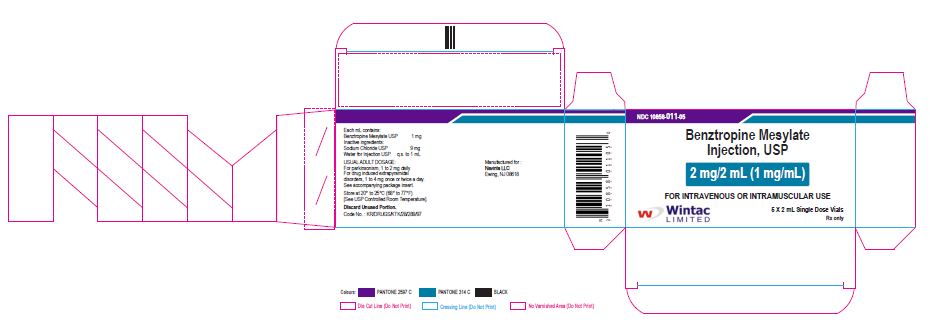 DRUG LABEL: benztropine mesylate
NDC: 10858-011 | Form: INJECTION
Manufacturer: Wintac Limited
Category: prescription | Type: HUMAN PRESCRIPTION DRUG LABEL
Date: 20201126

ACTIVE INGREDIENTS: BENZTROPINE MESYLATE 1 mg/1 mL
INACTIVE INGREDIENTS: SODIUM CHLORIDE; WATER

Benztropine mesylate injection, USP

PACKAGE LABEL.PRINCIPAL DISPLAY PANEL

NDC-10858-011-01

Benztropine Mesylate

Injection, USP

2 mg/2 mL (1 mg/mL)

For Intravenous or Intramuscular use

2 mL Single Dose Vial

Wintac Limited

Rx only

vial

NDC 10858-011-05

Benztropine Mesylate

Injection, USP

2 mg/2 mL (1 mg/mL)

FOR INTRAVENOUS OR INTRAMUSCULAR USE

Wintac Limited

5 X 2 mL Single Dose Vials

Rx only

carton